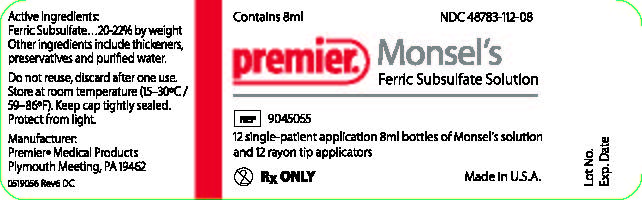 DRUG LABEL: Monsels Solution
NDC: 48783-112 | Form: PASTE
Manufacturer: Premier Dental Products Company
Category: prescription | Type: HUMAN PRESCRIPTION DRUG LABEL
Date: 20260113

ACTIVE INGREDIENTS: FERRIC SUBSULFATE 210 mg/1 g
INACTIVE INGREDIENTS: SILICON DIOXIDE; FERRIC SULFATE; SODIUM BENZOATE; WATER

Monsels

Active Ingredients:

Ferric Subsulfate...20-22% by weight

INACTIVE INGREDIENT

Other ingredients include thickeners, preservatives and purified water.

DOSAGE AND ADMINISTRATION

Do not reuse, discard after one use.

STORAGE AND HANDLING

Store at room temperature (15-30°C).

Keep cap tightly sealed.

Protect from light.

Mfg. for and Dist. by:

Premier Medical Products

Plymouth Meeting, PA 19462

PRINCIPAL DISPLAY PANEL

Contains 8ml NDC 48783-112-08

Premier

Monsel's Ferric Subsulfate Solution

REF 9045055

12 single application 8ml bottles of Monsel's soution
and 12 rayon tip applicators

Rx ONLY Made in U.S.A.